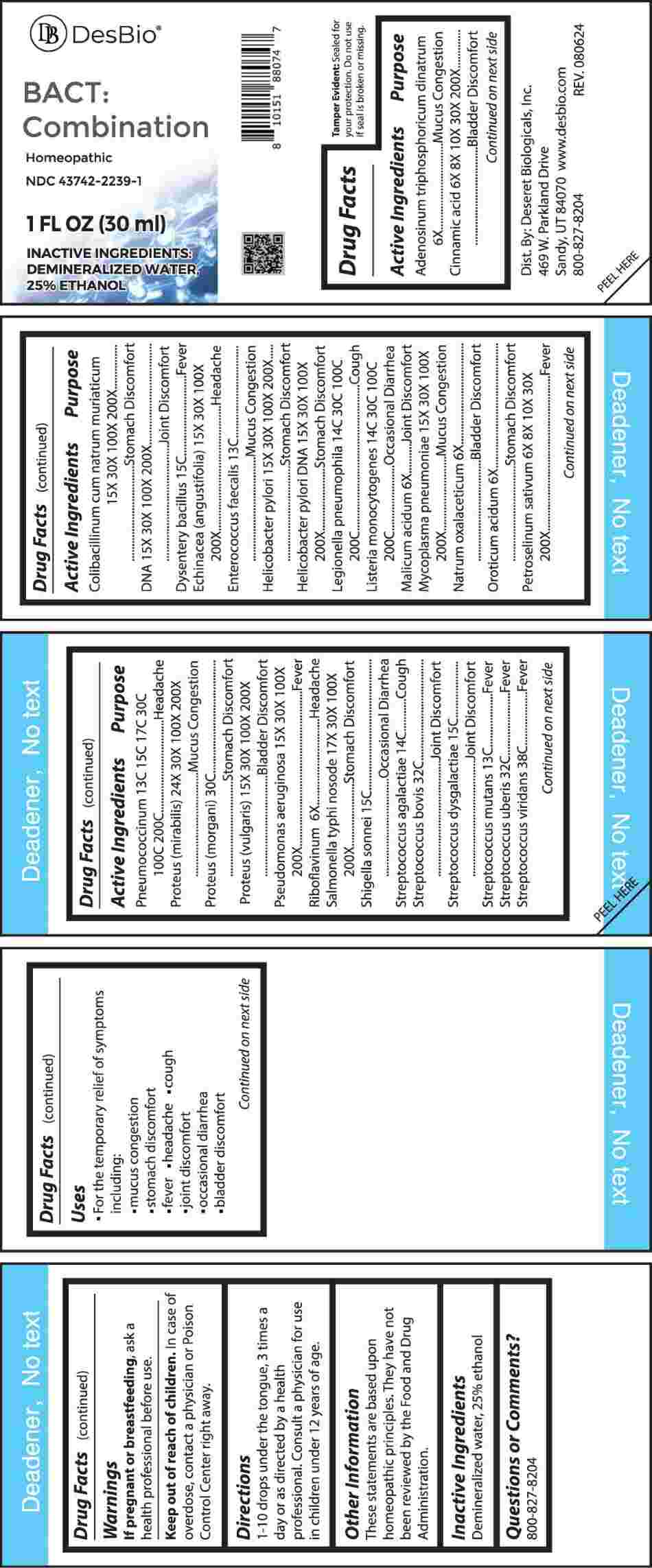 DRUG LABEL: Bact Combination
NDC: 43742-2239 | Form: LIQUID
Manufacturer: Deseret Biologicals, Inc.
Category: homeopathic | Type: HUMAN OTC DRUG LABEL
Date: 20241118

ACTIVE INGREDIENTS: ADENOSINE TRIPHOSPHATE DISODIUM 6 [hp_X]/1 mL; CINNAMIC ACID 6 [hp_X]/1 mL; ESCHERICHIA COLI 15 [hp_X]/1 mL; HERRING SPERM DNA 15 [hp_X]/1 mL; SHIGELLA DYSENTERIAE 15 [hp_C]/1 mL; ECHINACEA ANGUSTIFOLIA WHOLE 15 [hp_X]/1 mL; ENTEROCOCCUS FAECALIS 13 [hp_C]/1 mL; HELICOBACTER PYLORI 15 [hp_X]/1 mL; HELICOBACTER PYLORI DNA 15 [hp_X]/1 mL; LEGIONELLA PNEUMOPHILA 14 [hp_C]/1 mL; LISTERIA MONOCYTOGENES 14 [hp_C]/1 mL; MALIC ACID 6 [hp_X]/1 mL; MYCOPLASMA PNEUMONIAE 15 [hp_X]/1 mL; SODIUM DIETHYL OXALACETATE 6 [hp_X]/1 mL; OROTIC ACID MONOHYDRATE 6 [hp_X]/1 mL; PETROSELINUM CRISPUM WHOLE 6 [hp_X]/1 mL; STREPTOCOCCUS PNEUMONIAE 13 [hp_C]/1 mL; PROTEUS MIRABILIS 24 [hp_X]/1 mL; PROTEUS MORGANII 30 [hp_C]/1 mL; PROTEUS VULGARIS 15 [hp_X]/1 mL; PSEUDOMONAS AERUGINOSA 15 [hp_X]/1 mL; RIBOFLAVIN 6 [hp_X]/1 mL; SALMONELLA ENTERICA ENTERICA SEROVAR TYPHI 17 [hp_X]/1 mL; SHIGELLA SONNEI 15 [hp_C]/1 mL; STREPTOCOCCUS AGALACTIAE 14 [hp_C]/1 mL; STREPTOCOCCUS EQUINUS 32 [hp_C]/1 mL; STREPTOCOCCUS DYSGALACTIAE 15 [hp_C]/1 mL; STREPTOCOCCUS MUTANS 13 [hp_C]/1 mL; STREPTOCOCCUS UBERIS 32 [hp_C]/1 mL; STREPTOCOCCUS VIRIDANS GROUP 38 [hp_C]/1 mL
INACTIVE INGREDIENTS: WATER; ALCOHOL

DRUG FACTS:

ACTIVE INGREDIENTS:

Adenosinum Triphosphoricum Dinatrum 6X, Cinnamic Acid 6X, 8X, 10X, 30X, 200X, Colibacillinum Cum Natrum Muriaticum 15X, 30X, 100X, 200X, DNA 15X, 30X, 100X, 200X, Dysentery Bacillus 15C, Echinacea (Angustifolia) 15X, 30X, 100X, 200X, Enterococcus Faecalis 13C, Helicobacter Pylori 15X, 30X, 100X, 200X, Helicobacter Pylori DNA 15X, 30X, 100X, 200X, Legionella Pneumophila 14C, 30C, 100C, 200C, Listeria Monocytogenes 14C, 30C, 100C, 200C, Malicum Acidum 6X, Mycoplasma Pneumoniae 15X, 30X, 100X, 200X, Natrum Oxalaceticum 6X, Oroticum Acidum 6X, Petroselinum Sativum 6X, 8X, 10X, 30X, 200X, Pneumococcinum 13C, 15C, 17C, 30C, 100C, 200C, Proteus (Mirabilis) 24X, 30X, 100X, 200X, Proteus (Morgani) 30C, Proteus (Vulgaris) 15X, 30X, 100X, 200X, Pseudomonas Aeruginosa 15X, 30X, 100X, 200X, Riboflavinum 6X, Salmonella Typhi Nosode 17X, 30X, 100X, 200X, Shigella Sonnei 15C, Streptococcus Agalactiae 14C, Streptococcus Bovis 32C, Streptococcus Dysgalactiae 15C, Streptococcus Mutans 13C, Streptococcus Uberis 32C, Streptococcus Viridans 38C.

PURPOSE:

Adenosinum Triphosphoricum Dinatrum – Mucus Congestion, Cinnamic Acid – Bladder Discomfort, Colibacillinum Cum Natrum Muriaticum – Stomach Discomfort, DNA – Joint Discomfort, Dysentery Bacillus - Fever, Echinacea (Angustifolia) - Headache, Enterococcus Faecalis – Mucus Congestion, Helicobacter Pylori – Stomach Discomfort, Helicobacter Pylori DNA – Stomach Discomfort, Legionella Pneumophila - Cough, Listeria Monocytogenes – Occasional Diarrhea, Malicum Acidum – Joint Discomfort, Mycoplasma Pneumoniae – Mucus Congestion, Natrum Oxalaceticum – Bladder Discomfort, Oroticum Acidum – Stomach Discomfort, Petroselinum Sativum - Fever, Pneumococcinum - Headache, Proteus (Mirabilis) – Mucus Congestion, Proteus (Morgani) – Stomach Discomfort, Proteus (Vulgaris) – Bladder Discomfort, Pseudomonas Aeruginosa - Fever, Riboflavinum - Headache, Salmonella Typhi Nosode – Stomach Discomfort, Shigella Sonnei – Occasional Diarrhea, Streptococcus Agalactiae - Cough, Streptococcus Bovis – Joint Discomfort, Streptococcus Dysgalactiae – Joint Discomfort, Streptococcus Mutans - Fever, Streptococcus Uberis - Fever, Streptococcus Viridans - Fever

USES:

• For the temporary relief of symptoms including:
• mucus congestion
• stomach discomfort
• fever • headache • cough
• joint discomfort
• occasional diarrhea
• bladder discomfort

These statements are based upon homeopathic principles. They have not been reviewed by the Food and Drug Administration.

WARNINGS:

If pregnant or breast-feeding, ask a health professional before use.

Keep out of reach of children. In case of overdose, contact a physician or Poison Control Center right away.

Tamper Evident: Sealed for your protection. Do not use if seal is broken or missing.

KEEP OUT OF REACH OF CHILDREN:

In case of overdose, contact a physician or Poison Control Center right away.

DIRECTIONS:

1-10 drops under the tongue, 3 times a day or as directed by a health professional. Consult a physician for use in children under 12 years of age.

INACTIVE INGREDIENTS:

Demineralized water, 25% ethanol

QUESTIONS:

Dist. By: Deseret Biologicals, Inc.

469 W. Parkland Drive

Sandy, UT 84070

www.desbio.com

800-827-8204

PACKAGE LABEL DISPLAY:

DesBio

BACT: Combination

Homeopathic

NDC 43742-2239-1

1 FL OZ (30ml)